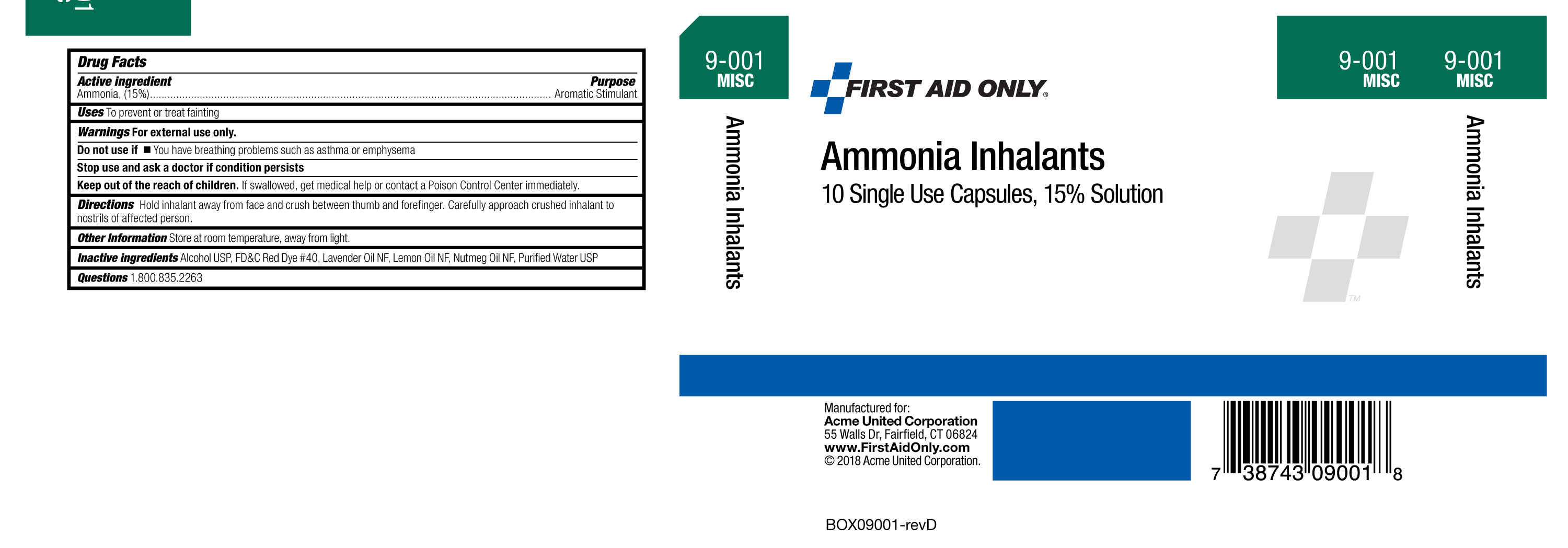 DRUG LABEL: First Aid Only Ammonia Inhalants
NDC: 0924-5401 | Form: INHALANT
Manufacturer: Acme United Corporation
Category: otc | Type: HUMAN OTC DRUG LABEL
Date: 20180219

ACTIVE INGREDIENTS: AMMONIA 0.045 g/0.3 mL
INACTIVE INGREDIENTS: LEMON OIL; WATER; LAVENDER OIL; ALCOHOL; FD&C RED NO. 40; NUTMEG OIL

Ammonia Inhalants

Active Ingredient

Ammonia(15%)

Purpose

Aromatic Stimulant

INDICATIONS AND USAGE

Uses To prevent or treat fainting

Warnings For external use only.

Do not use •If you have breathing problems such as asthma or emphysema

Stop use and ask a doctor if condition persists

KEEP OUT OF REACH OF CHILDREN

Keep out of the reach of children. If swallowed, get medical help or contact a Poison Control Center immediately

DOSAGE AND ADMINISTRATION

Directions Hold inhalant away from face and crush between thumb and forefinger. Carefully approach crushed inhalant to nostrils of affected person.

Other Information Store at room temperarure, away from light

INACTIVE INGREDIENT

Inactive Ingredients Alcohol USP, FD&C Red Dye #40, Lavender Oil NF, Lemon Oil NF, Nutmeg Oil NF, Purified Water USP

Questions 1.800.835.2263